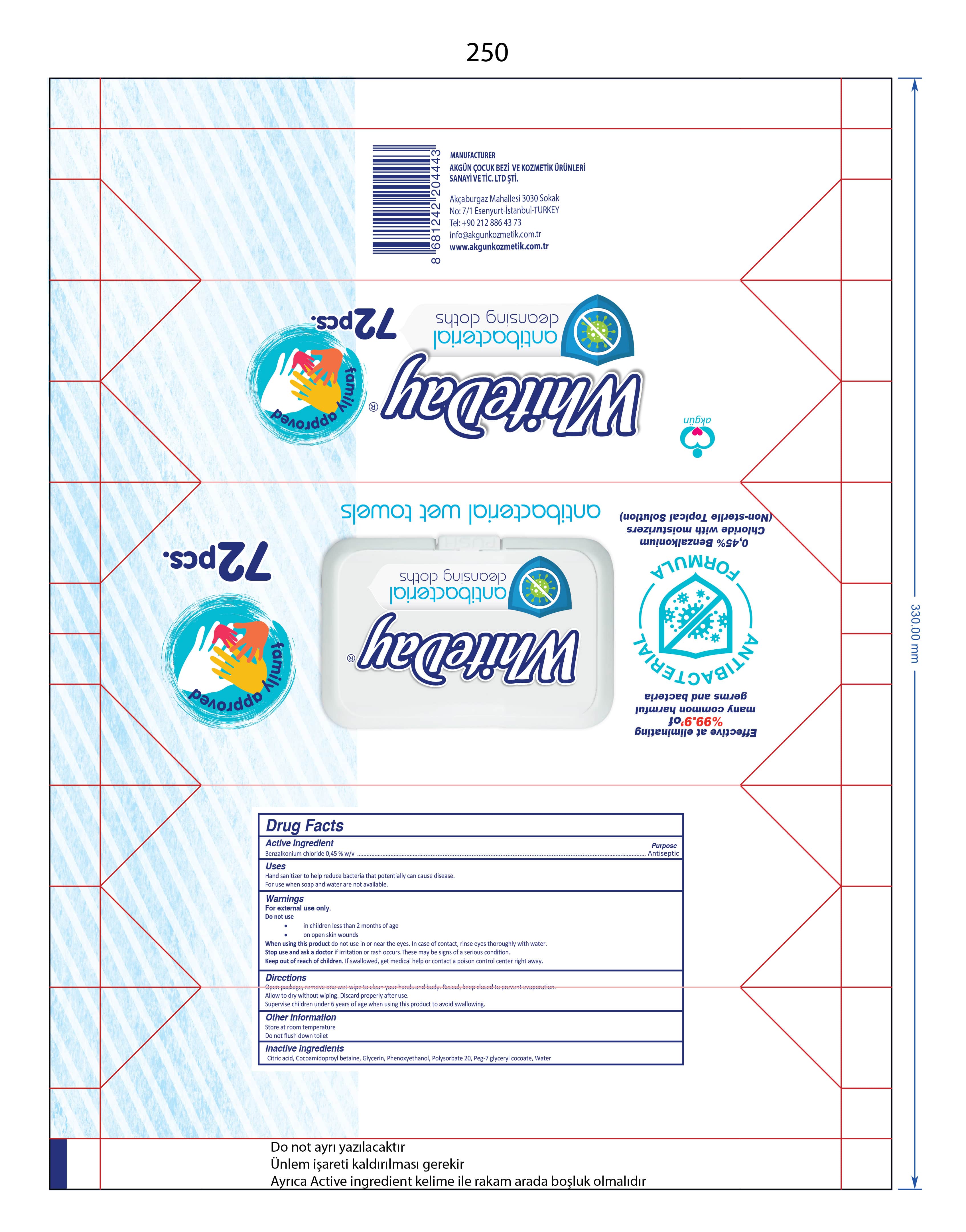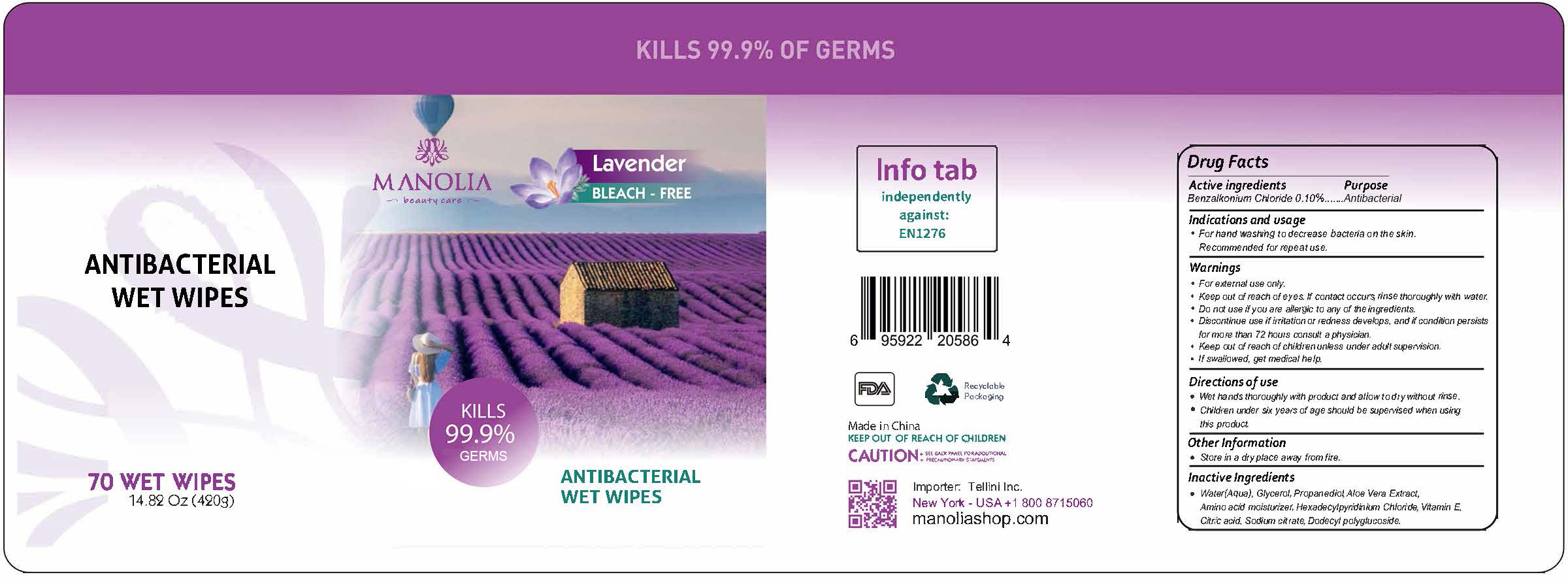 DRUG LABEL: Manolia Antibacterial Wet Wipe
NDC: 80887-007 | Form: CLOTH
Manufacturer: TELLINI INC.
Category: otc | Type: HUMAN OTC DRUG LABEL
Date: 20201205

ACTIVE INGREDIENTS: BENZALKONIUM CHLORIDE 0.1 g/100 g
INACTIVE INGREDIENTS: CHLORPHENESIN 0.05 g/100 g; PROPANEDIOL 0.2 g/100 g; BETAINE 0.1 g/100 g; GLYCEROL FORMAL 0.5 g/100 g; WATER 98.81 g/100 g; FRAGRANCE LAVENDER ORC1800979 0.1 g/100 g; CETYLPYRIDINIUM CHLORIDE ANHYDROUS 0.05 g/100 g; ANHYDROUS CITRIC ACID 0.02 g/100 g

Manolia Antibacterial Wet Wipe

This is a hand sanitizer manufactured according to the Temporary Policy for Preparation of Certain Alcohol-Based Hand Sanitizer Products During the Public Health Emergency (CoViD-19); Guidance for Industry.

The hand sanitizer is manufactured using only the following United States Pharmacopoeia (USP) grade ingredients in the preparation of the product (percentage in final product formulation) consistent with World Health Organization (WHO) recommendations:

1. Benzalkonium Chloride (0.45%, volume/volume (w/v)) in an aqueous solution.
2. Glycerol (0.8% w/v).
3. Phenoxyethanol (0.1% w/v).
4. Cocamidopropyl Betaine (0.4% w/v).
5. Polysorbate 20 (0.2% w/v).
6. Peg-7 Glyceryl Cocoate (0.3% w/v).
7. Citric Acid (0.1% w/v).
8. Sterile distilled water or boiled cold water.

The firm does not add other active or inactive ingredients. Different or additional ingredients may impact the quality and potency of the product.

Active Ingredient(s)

Benzalkonium Chloride 0.45% w/v. Purpose: Antiseptic

Purpose

Antiseptic, Hand Sanitizer

Use

Hand Sanitizer to help reduce bacteria that potentially can cause disease. For use when soap and water are not available.

Warnings

For external use only.

Do not use

- in children less than 2 months of age
- on open skin wounds

When using this product keep out of eyes. In case of contact with eyes, rinse eyes thoroughly with water.
Stop use and ask a doctor if irritation or rash occurs. These may be signs of a serious condition.
Keep out of reach of children. If swallowed, get medical help or contact a Poison Control Center right away.

Stop use and ask a doctor if irritation or rash occurs. These may be signs of a serious condition.

Keep out of reach of children. If swallowed, get medical help or contact a Poison Control Center right away.

Directions

- Open package, remove one wet wipes to clean your hands and body. Reseal, keep closed to prevent evaporation.
- Allow to dry without wiping. Discard properly after use.
- Supervise children under 6 years of age when using this product to avoid swallowing.

Other information

- Store at room temperature.
- Do not flush down toilet.

Inactive ingredients

Citric acid, Cocoamidopropyl betaine, glycerin, Phenoxyethanol, Polysorbate 20, Peg-7 glyceryl cocoate, purified water USP

Package Label - Principal Display Panel

72 pcs NDC: 86812-002-01